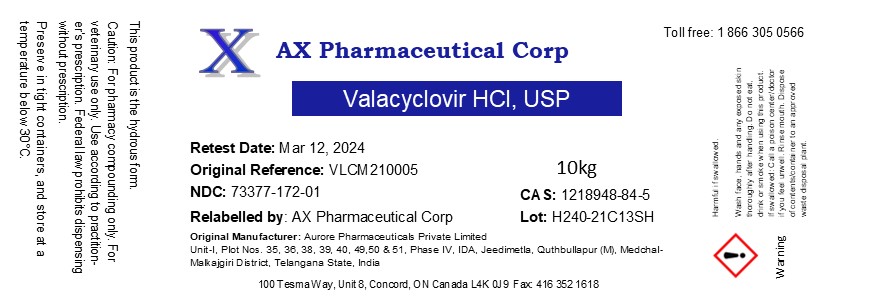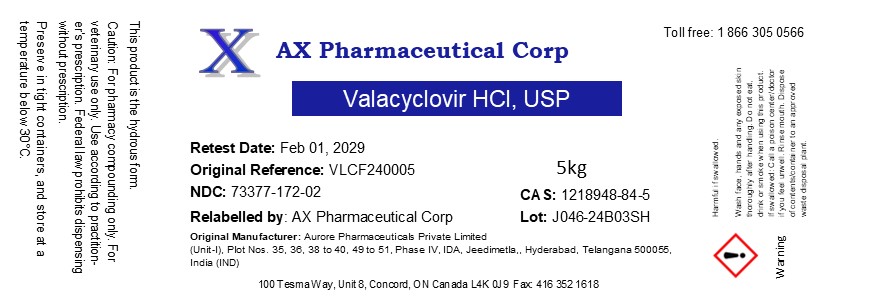 DRUG LABEL: Valacyclovir HCl
NDC: 73377-172 | Form: POWDER
Manufacturer: AX Pharmaceutical Corp
Category: other | Type: BULK INGREDIENT - ANIMAL DRUG
Date: 20240415

ACTIVE INGREDIENTS: VALACYCLOVIR HYDROCHLORIDE MONOHYDRATE 1 g/1 g

Valacyclovir HCl